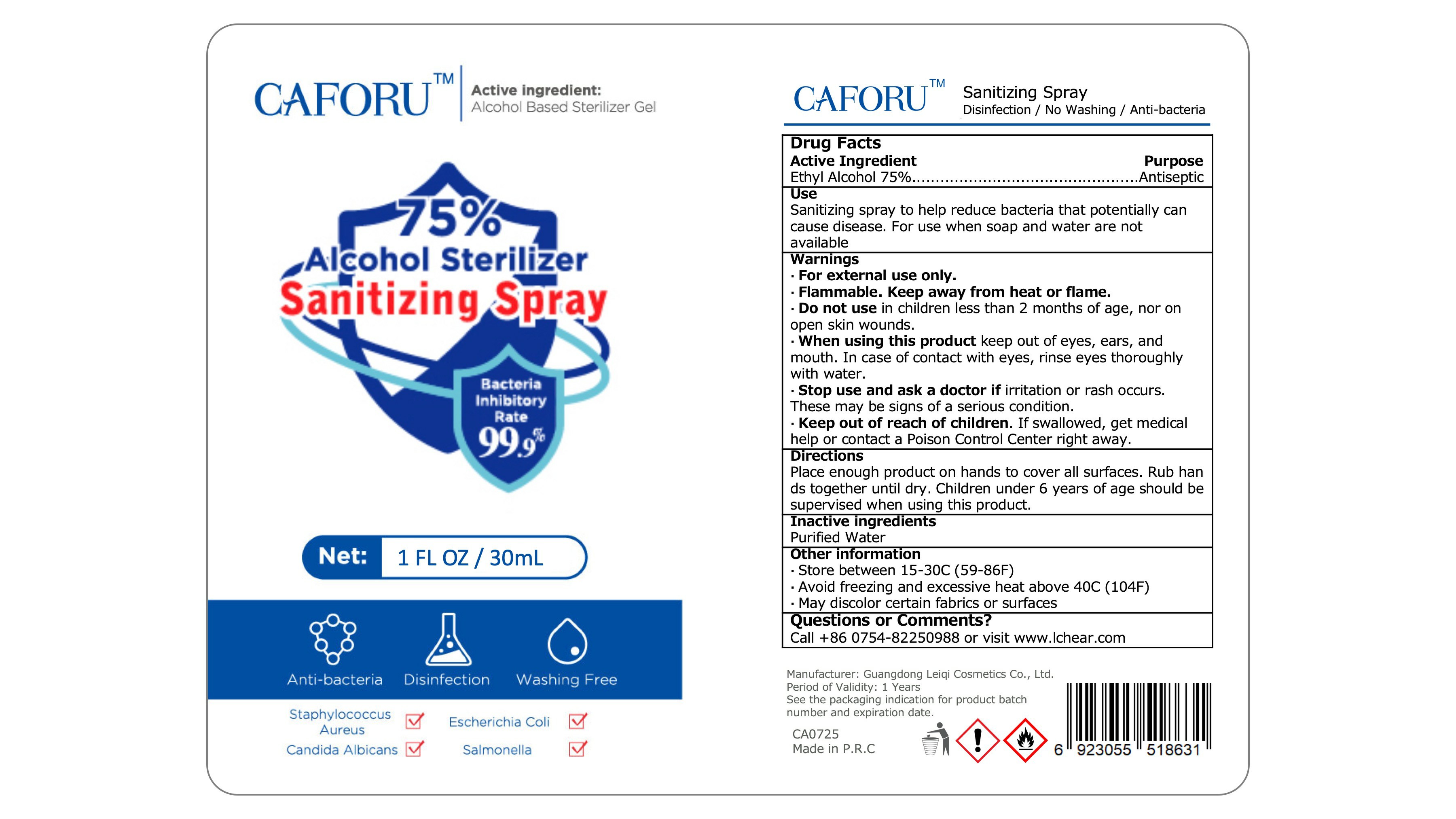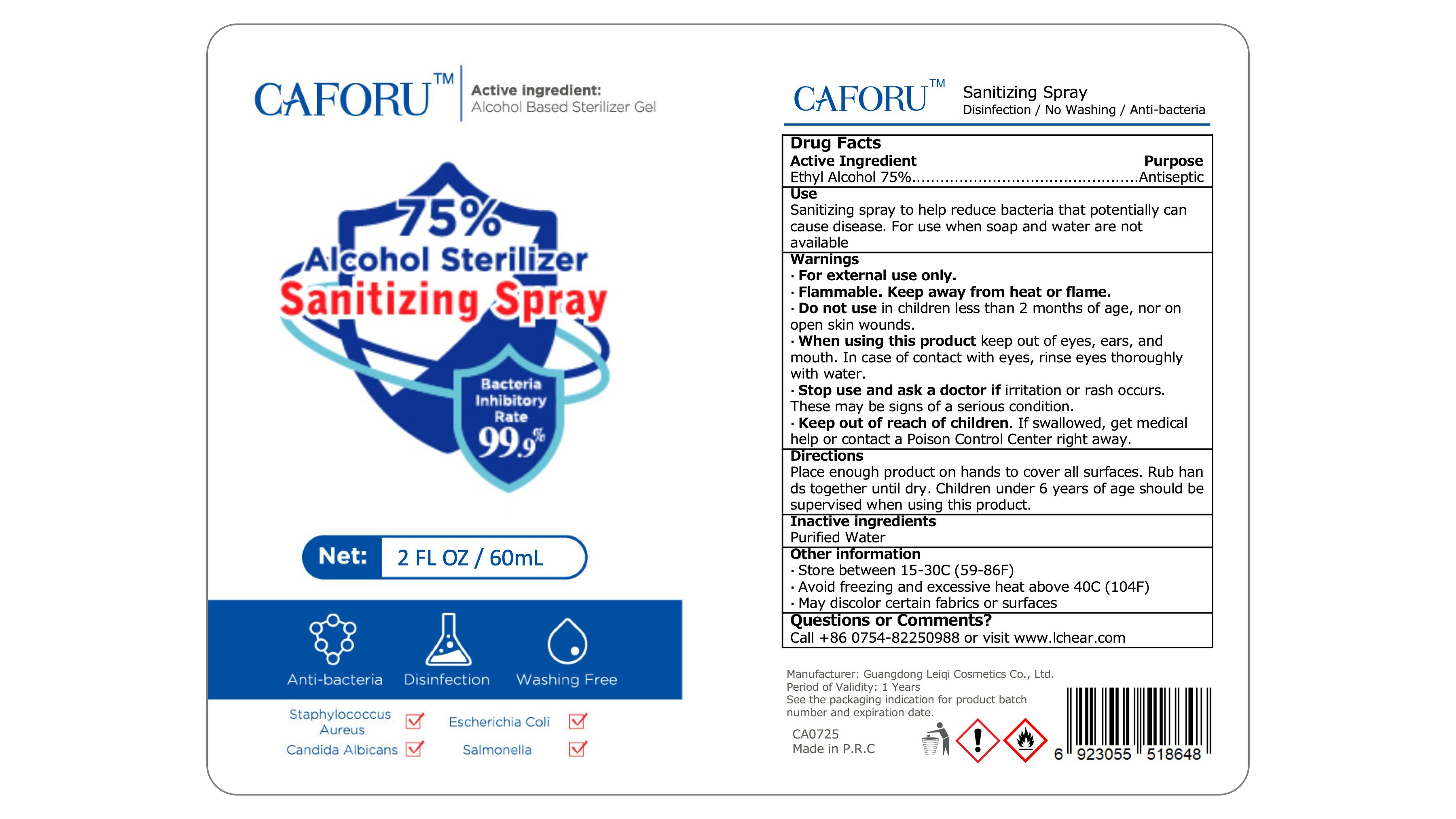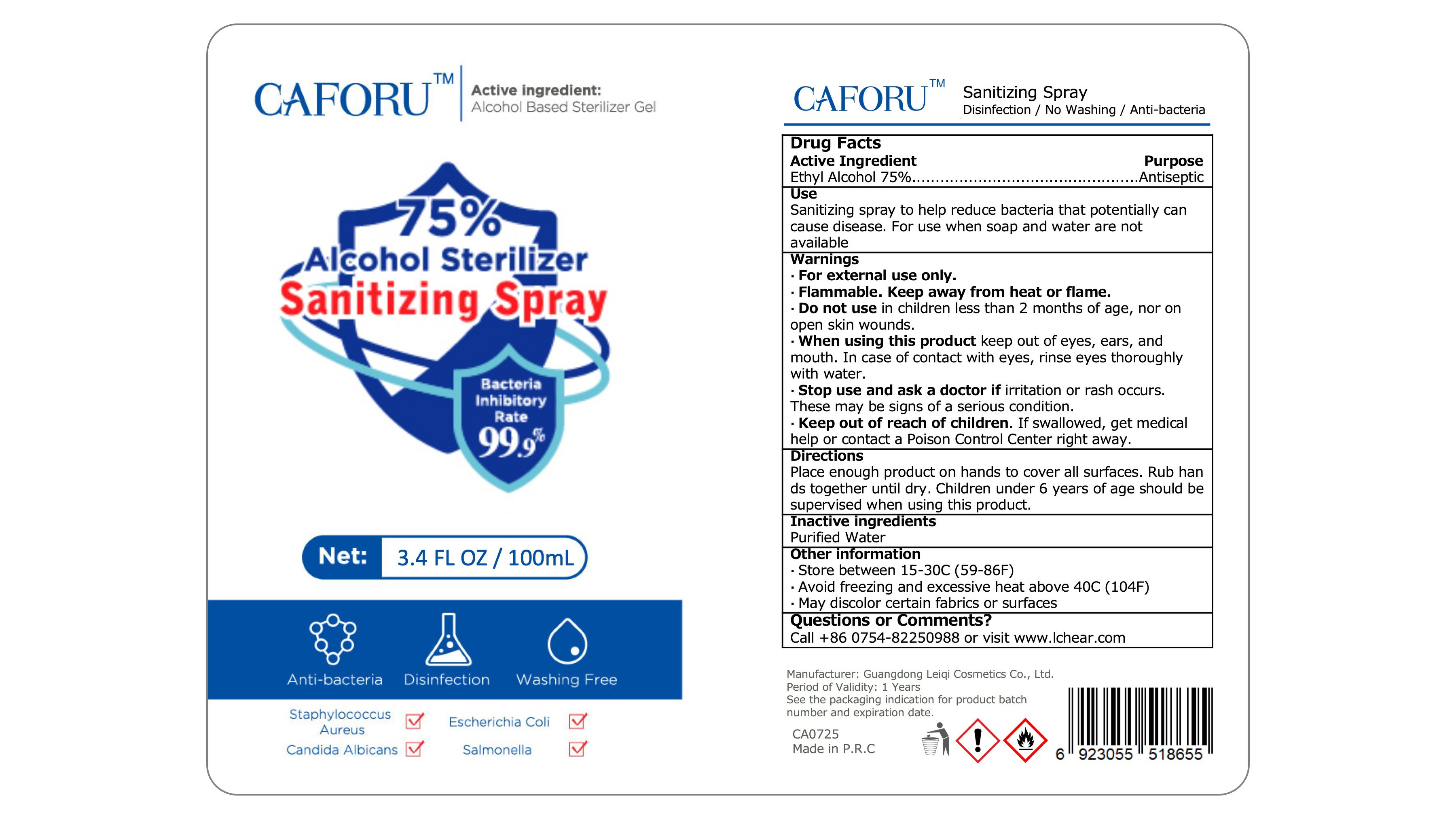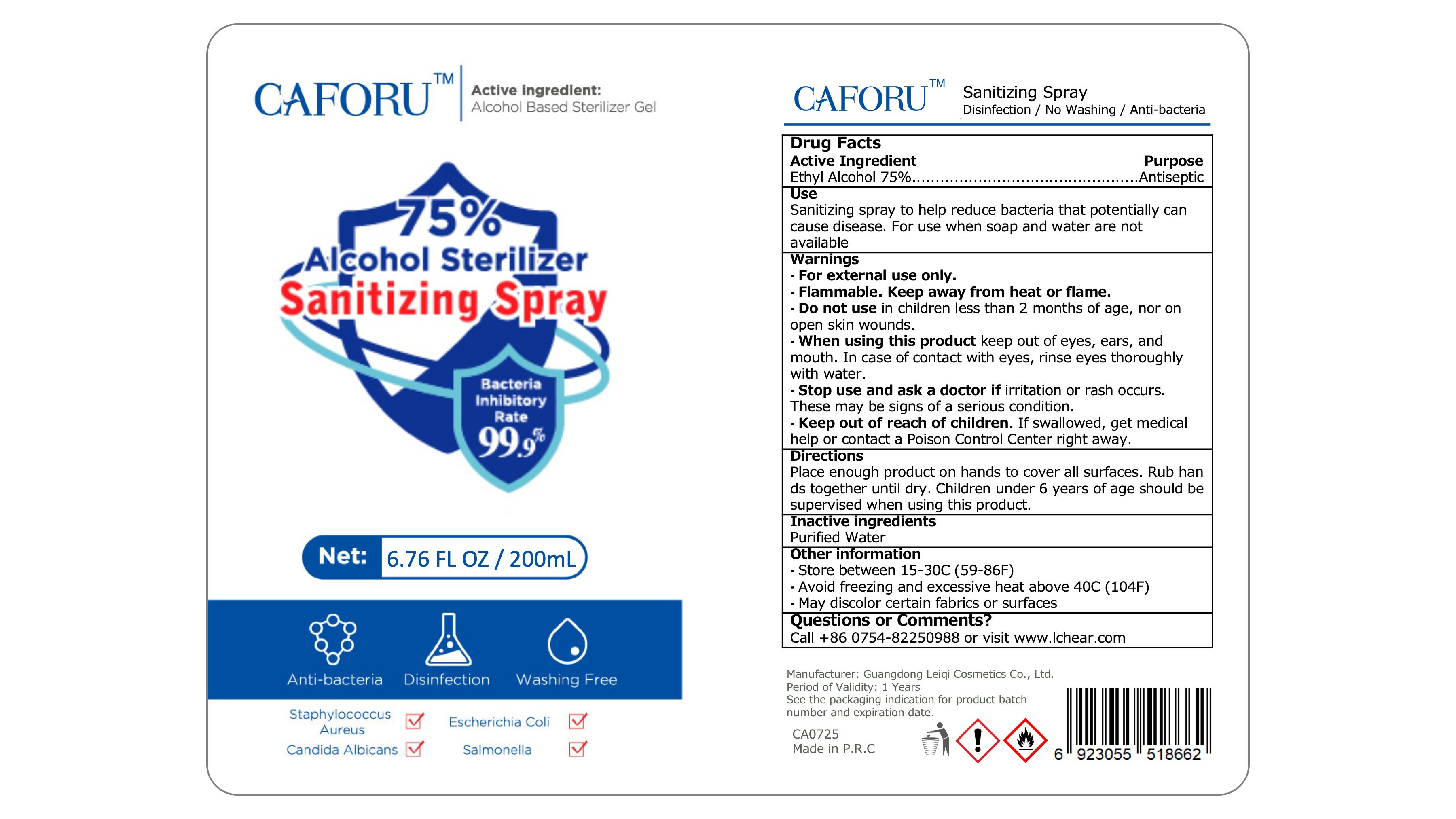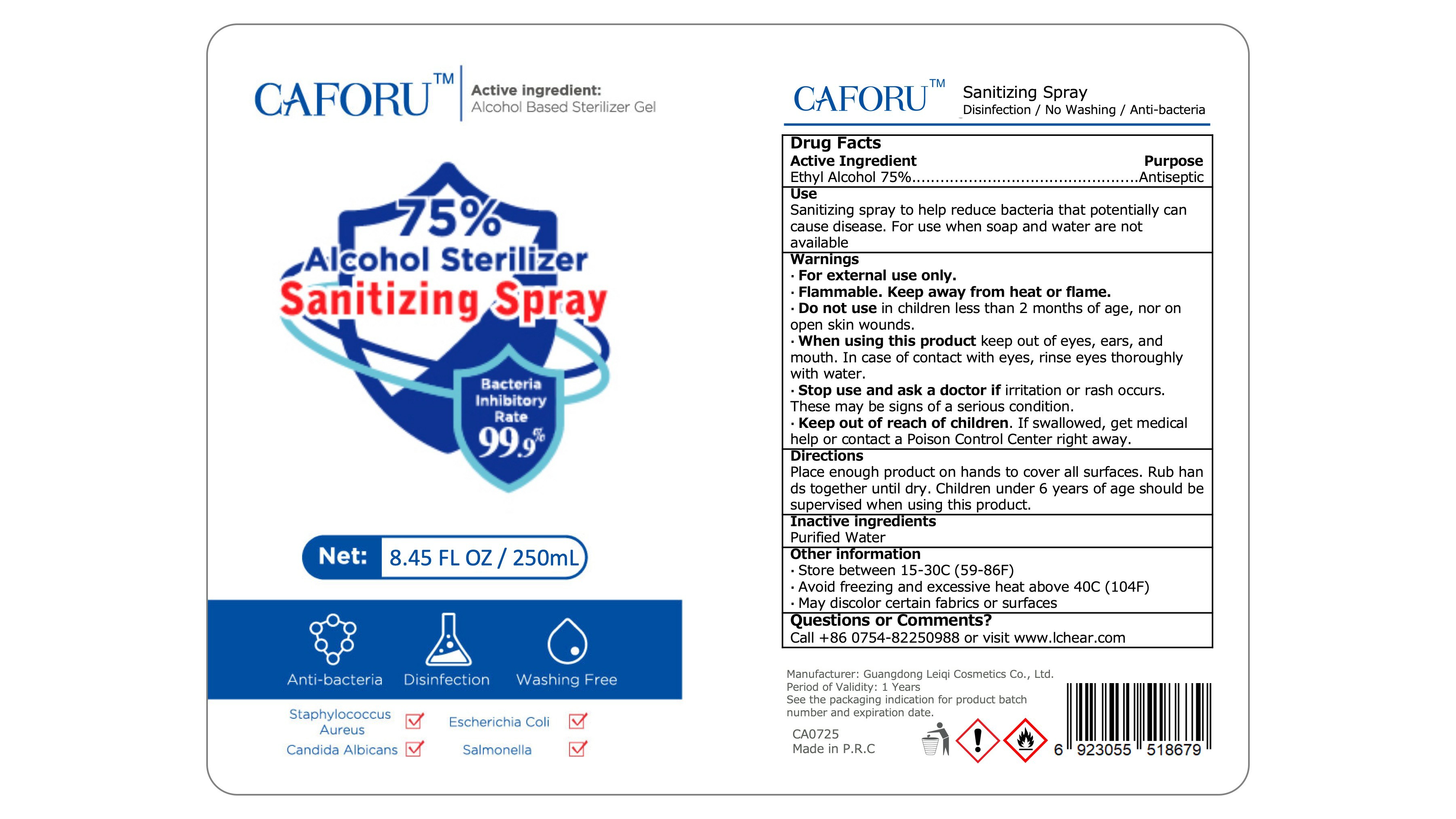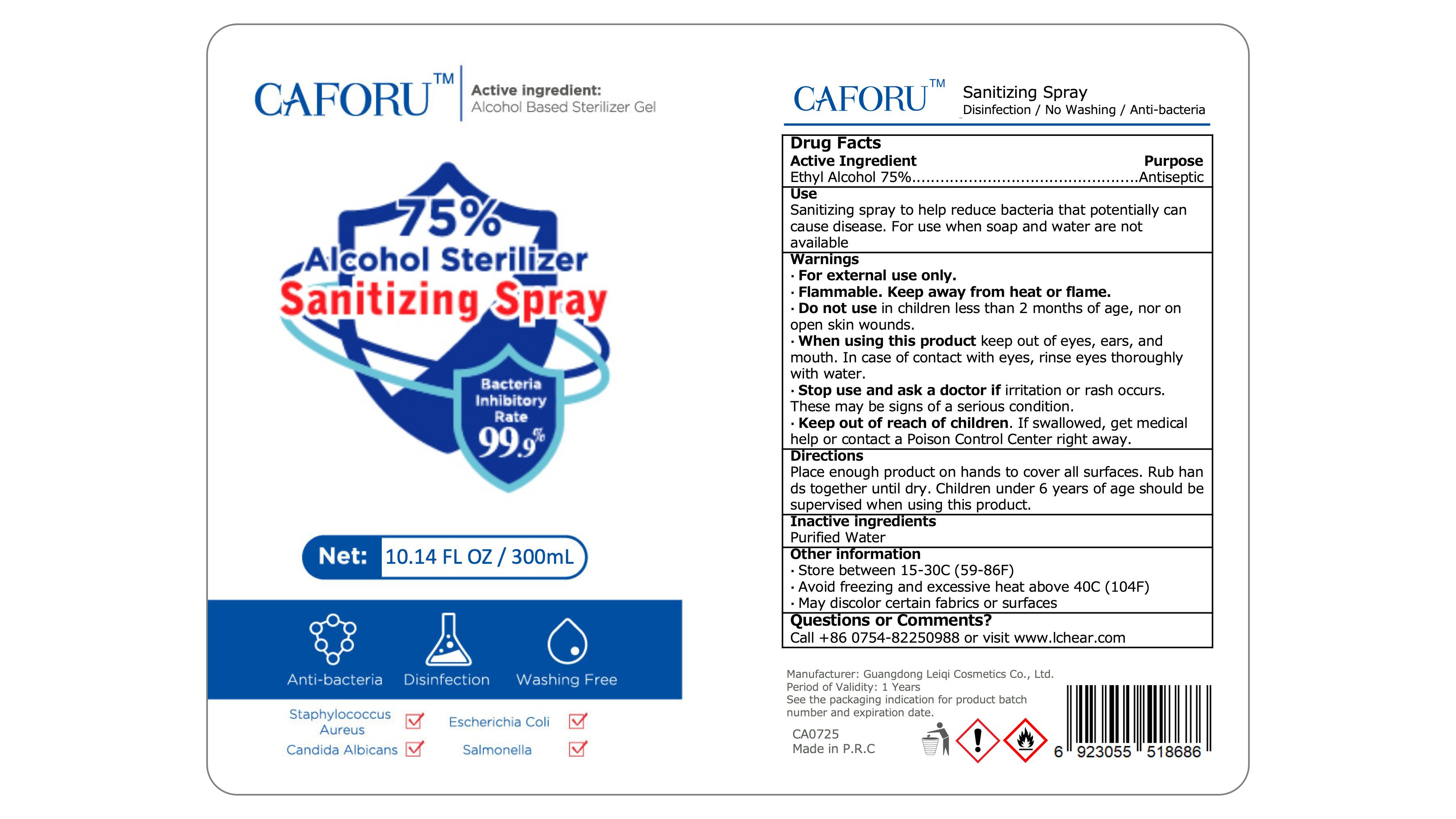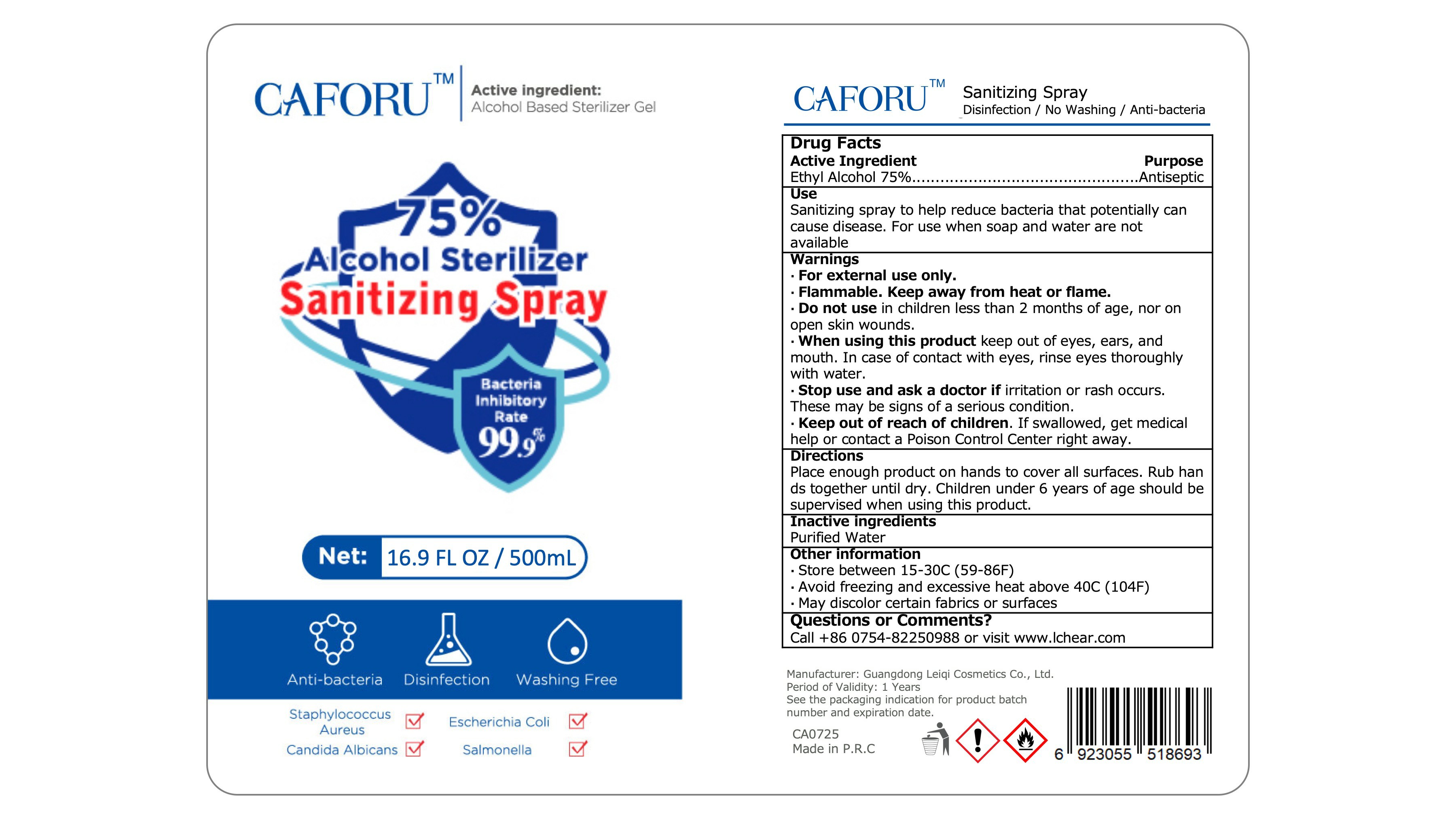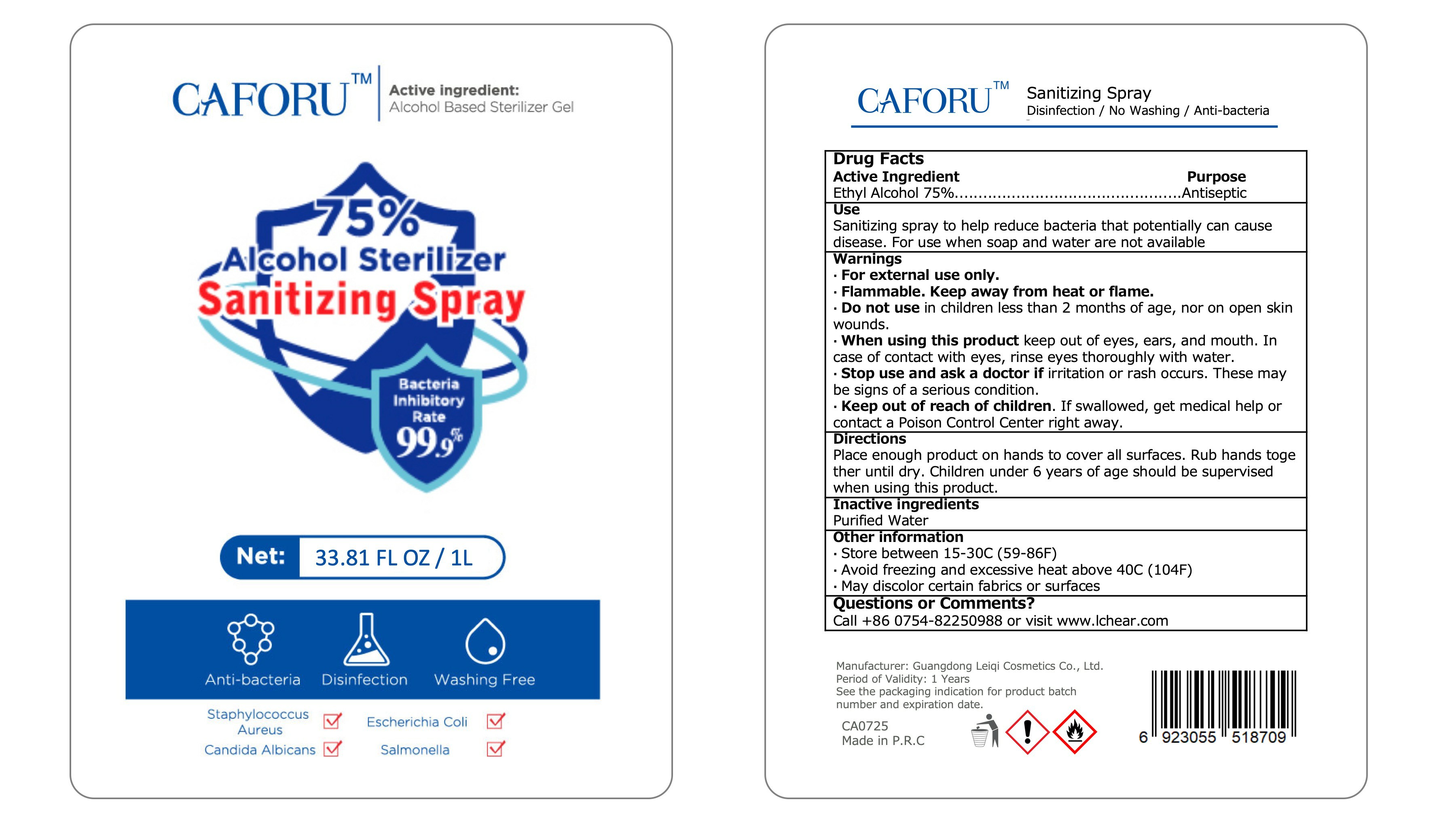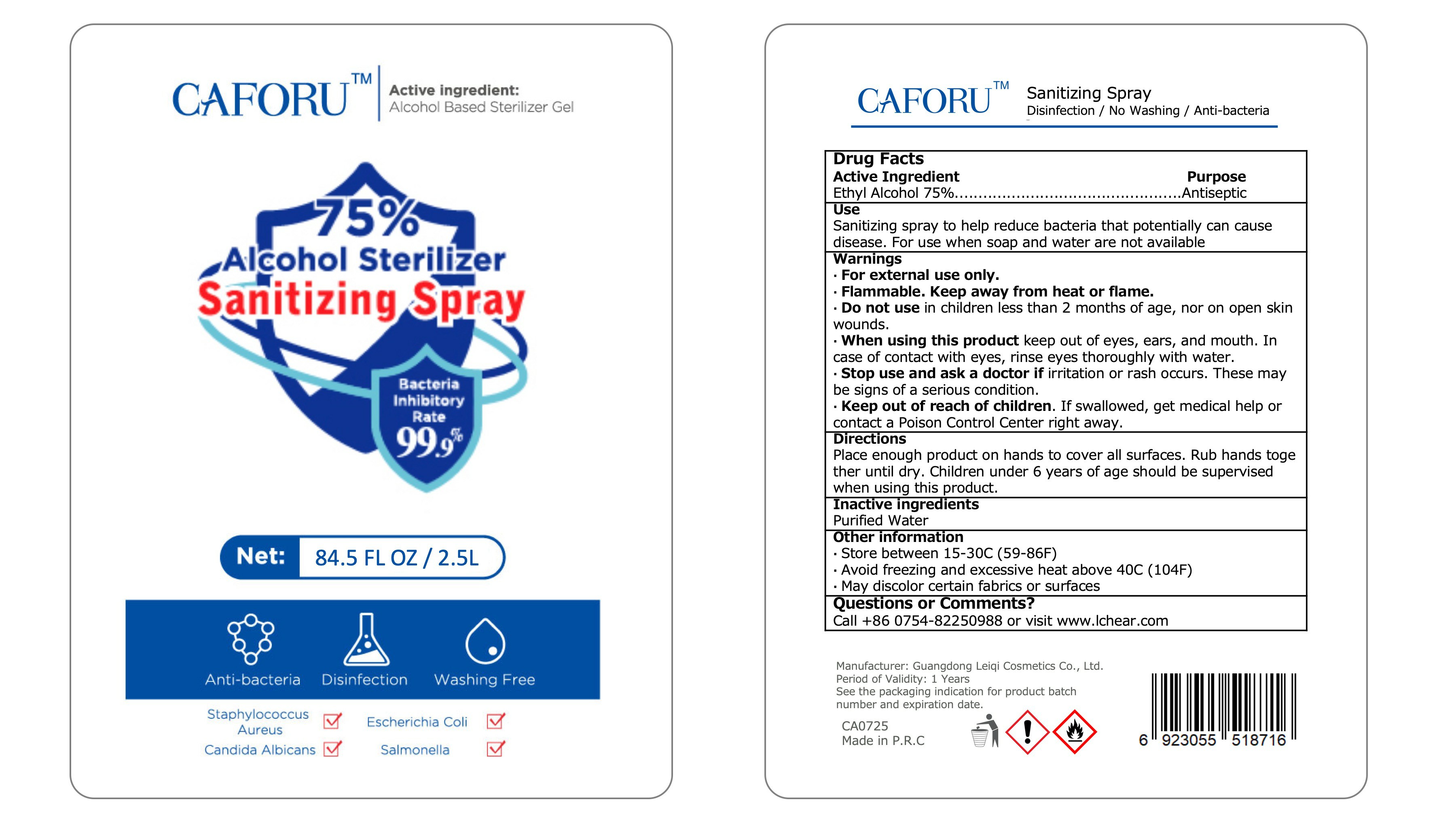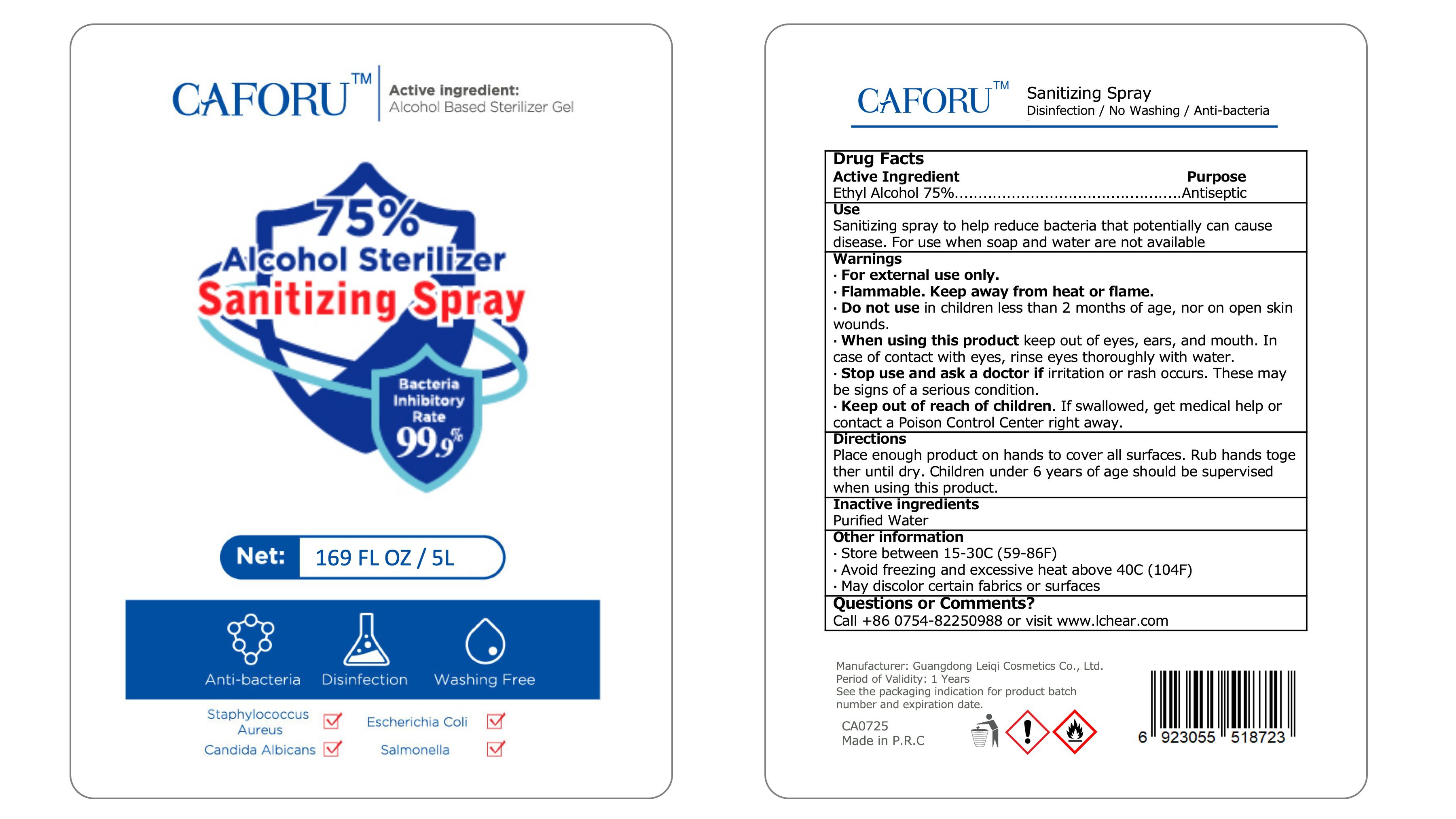 DRUG LABEL: Sanitizing
NDC: 79864-002 | Form: SPRAY
Manufacturer: guangdong leiqi cosmetic company ltd,.
Category: otc | Type: HUMAN OTC DRUG LABEL
Date: 20210114

ACTIVE INGREDIENTS: ALCOHOL 75 mL/100 mL
INACTIVE INGREDIENTS: WATER

79864-002
Sanitizing Spray

Active Ingredient(s)

Ethyl Alcohol 75%

Purpose

Antiseptic

Use

Sanitizing spray to help reduce bacteria that potentially can cause disease. For use when soap and water are not available

Do not use in children less than 2 months of age, nor on open skin wounds.

When using this product keep out of eyes, ears, and mouth. In case of contact with eyes, rinse eyes thoroughly with water.

Stop use and ask a doctor if irritation or rash occurs. These may be signs of a serious condition.

Keep out of reach of children. If swallowed, get medical help or contact a Poison Control Center right away.

Stop use and ask a doctor if irritation or rash occurs. These may be signs of a serious condition.

Keep out of reach of children. If swallowed, get medical help or contact a Poison Control Center right away.

Directions

Place enough product on hands to cover all surfaces. Rub hands together until dry. Children under 6 years of age should be supervised when using this product.

Other information

Store between 15-30C (59-86F)
Avoid freezing and excessive heat above 40C (104F)
May discolor certain fabrics or surfaces

Inactive ingredients

Purified Water